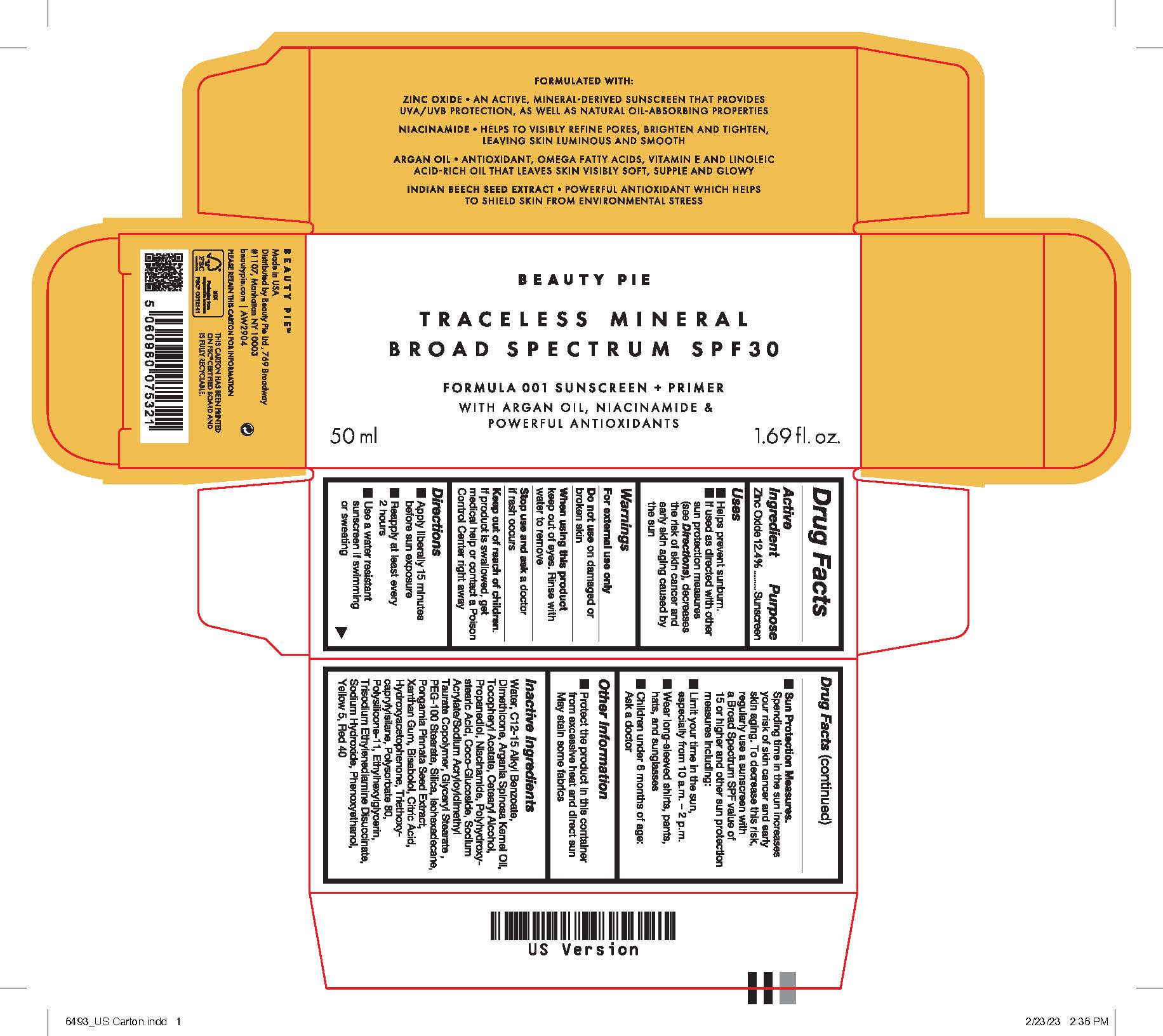 DRUG LABEL: TRACELESS MINERAL BROAD SPECTRUM SPF  SUNSCREEN AND PRIMER
NDC: 59735-990 | Form: CREAM
Manufacturer: MANA PRODUCTS, INC.
Category: otc | Type: HUMAN OTC DRUG LABEL
Date: 20240903

ACTIVE INGREDIENTS: ZINC OXIDE 12.4 g/100 g
INACTIVE INGREDIENTS: WATER; ALKYL (C12-15) BENZOATE; NIACINAMIDE; .ALPHA.-BISABOLOL, (+)-; XANTHAN GUM; DIMETHICONE/VINYL DIMETHICONE CROSSPOLYMER (SOFT PARTICLE); TRISODIUM ETHYLENEDIAMINE DISUCCINATE; SODIUM HYDROXIDE; FD&C RED NO. 40; DIMETHICONE 200; PROPANEDIOL; POLYHYDROXYSTEARIC ACID (2300 MW); COCO GLUCOSIDE; SODIUM ACRYLATE/SODIUM ACRYLOYLDIMETHYLTAURATE COPOLYMER (4000000 MW); GLYCERYL STEARATE SE; PEG-100 STEARATE; ISOHEXADECANE; ANHYDROUS CITRIC ACID; TRIETHOXYCAPRYLYLSILANE; HYDROXYACETOPHENONE; ARGAN OIL; POLYSORBATE 80; ETHYLHEXYLGLYCERIN; PHENOXYETHANOL; FD&C YELLOW NO. 5; ALPHA-TOCOPHEROL ACETATE; CETOSTEARYL ALCOHOL; SILICON DIOXIDE; PONGAMIA PINNATA SEED

BEAUTY PIE - TRACELESS MINERAL BROAD SPECTRUM SPF 30 SUNSCREEN + PRIMER

ACTIVE INGREDIENTS

Zinc Oxide 12.4%

PURPOSE

SUNSCREEN

USES

Helps prevent sunburn. If used as directed with other sun protection measures (see directions), decreases the risk of skin cancer and early skin aging caused by the sun.

WARNINGS

For external use, only. Do not use on damaged or broken skin. Stop use and ask doctor if rash occurs. When using, this product should be kept away from eye area. Rinse with water to remove.

Keep out of reach of children. If swallowed, get medical help or contact a Poison Control Center right away.

DIRECTIONS

Apply liberally 15 minutes before sun exposure. Use a water-resistant sunscreen if swimming or sweating. Reapply at least every 2 hours, Sun Protection Measures: Spending time in the sun increases risk of skin cancer and early aging. To decrease this risk, regularly use a sunscreen with a Broad-Spectrum SPF value of 15 or higher and other sun protection measures including: limit time in the sun especially from 10:00 a.m. - 2:00 p.m. Wear long sleeved shirts, pants, hats and sunglasses. Children under 6 months: ask a doctor.

OTHER INFORMATION

PROTECT THE PRODUCT IN THIS CONTAINER FROM EXCESSIVE HEAT AND DIRECT SUN. MAY STAIN SOME FABRICS

INACTIVE INGREDIENTS

Water,C12-15 Alkyl Benzoate,Dimethicone,Argania Spinosa Kernel Oil,Tocopheryl Acetate,Cetearyl Alcohol,Propanediol,
Niacinamide,Polyhydroxystearic acid,Coco-Glucoside,Sodium Acrylate/Sodium Acryloyldimethyl Taurate Copolymer ,Glyceryl Stearate ,PEG-100 Stearate ,Silica ,Isohexadecane ,Pongamia Pinnata Seed Extract ,Xanthan Gum ,Bisabolol ,Citric Acid ,Hydroxyacetophenone ,Triethoxycaprylylsilane,Polysorbate 80,Polysilicone-11 ,Ethylhexylglycerin ,Trisodium Ethylenediamine Disuccinate ,Sodium Hydroxide ,Phenoxyethanol ,Yellow 5,Red 40

RECENT MAJOR CHANGES

DOSAGE & ADMINISTRATION added